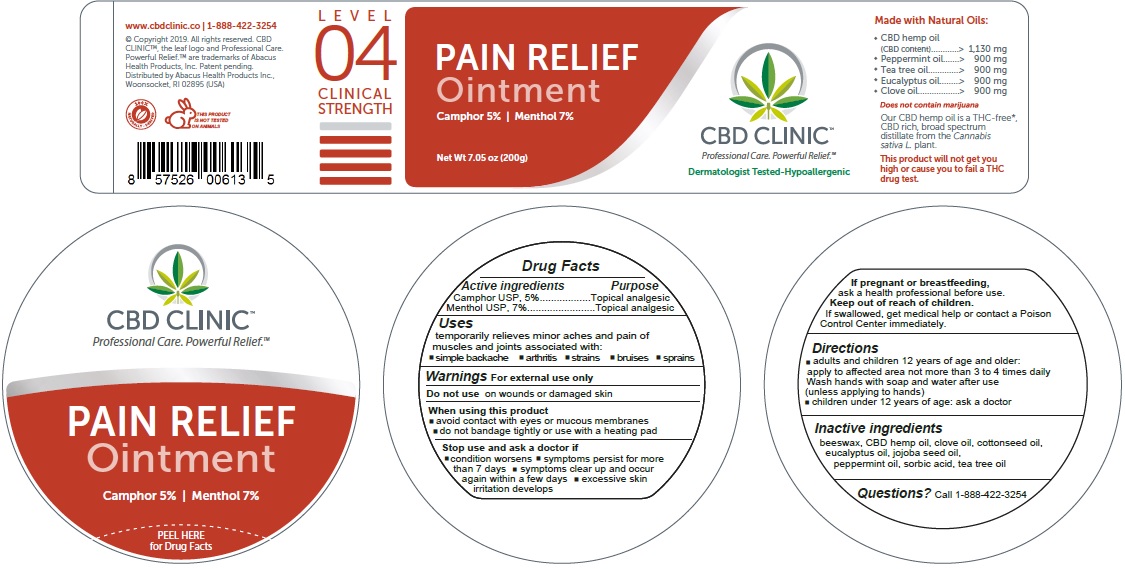 DRUG LABEL: CBD Clinic Pain Relief - Level 4
NDC: 73096-764 | Form: OINTMENT
Manufacturer: ABACUS HEALTH PRODUCTS, INC.
Category: otc | Type: HUMAN OTC DRUG LABEL
Date: 20250407

ACTIVE INGREDIENTS: MENTHOL 7 g/100 g; CAMPHOR (NATURAL) 5 g/100 g
INACTIVE INGREDIENTS: CLOVE OIL; COTTONSEED OIL; EUCALYPTUS OIL; HEMP; JOJOBA OIL; PEPPERMINT OIL; SORBIC ACID; TEA TREE OIL; WHITE WAX

CBD Clinic Pain Relief - Level 4

Active Ingredients

Menthol USP, 7%, Camphor USP, 5%

Purpose

Menthol, Camphor - Topical Analgesic

Uses

temporarily relieves minor aches and pain of muscles and joints associated with:
• simple backache • arthritis • strains • bruises • sprains

Warnings

For external use only
Do not use on
• wounds or damaged skin
When using this product
• avoid contact with eyes or mucous membranes
• do not bandage tightly or use with a heating pad
Stop use and ask a doctor if
• condition worsens
• symptoms persist for more than 7 days
• symptoms clear up and occur again within a few days
• excessive skin irritation develops
If pregnant or breast-feeding
ask a health professional before use
Keep out of reach of children
If swallowed, get medical help or contact a Poison Control Center immediately

Directions

• adults and children 12 years of age and older:
apply to affected area not more than 3 to 4 times daily
Wash hands with soap and water after use (unless applying to hands)
• children under 12 years of age: ask a doctor

Inactive Ingredients

beeswax, CBD hemp oil, clove oil, cottonseed oil, eucalyptus oil, jojoba seed oil, peppermint oil, sorbic acid, tea tree oil

Questions?

Call 1-888-422-3254